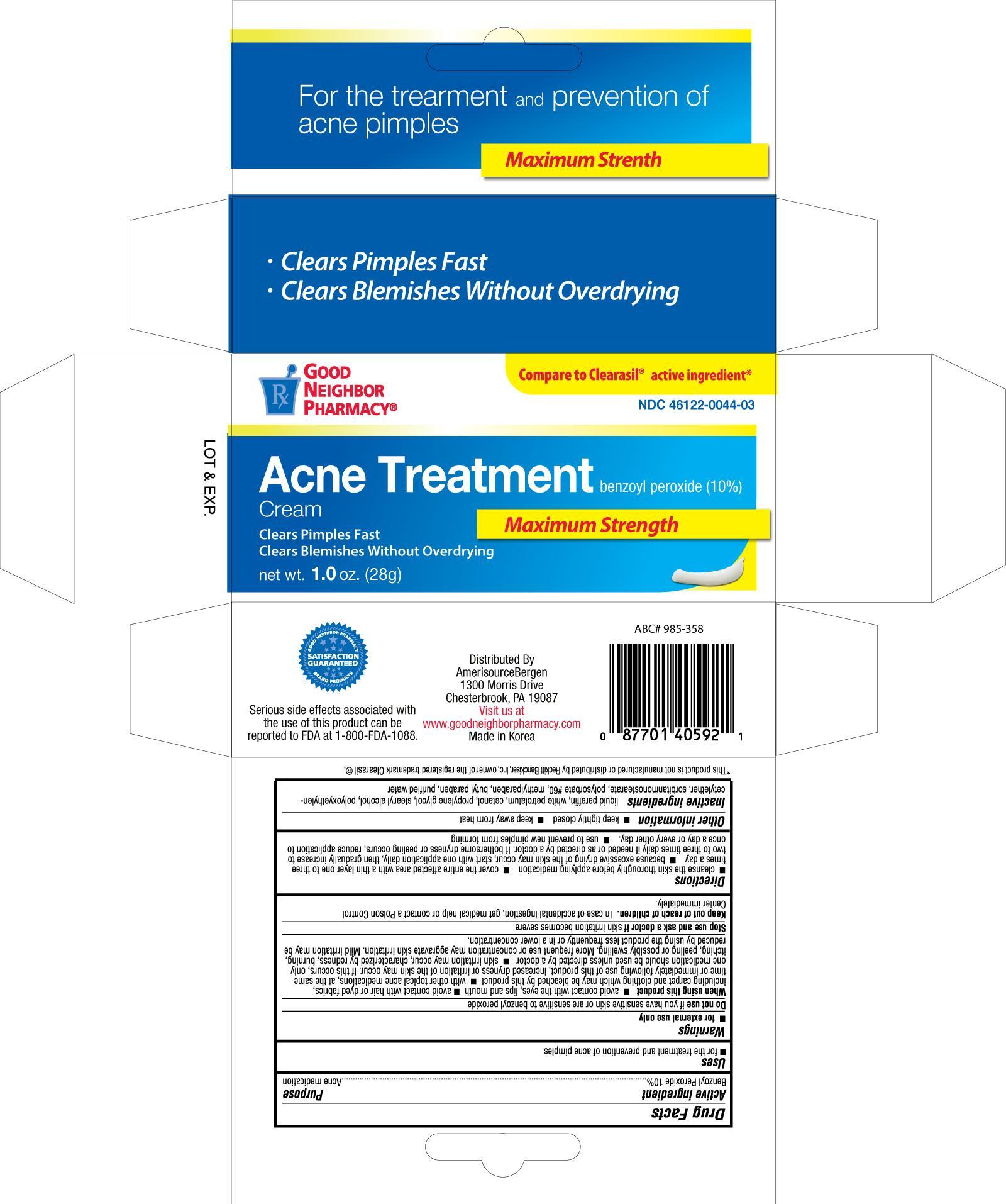 DRUG LABEL: GNP Acne Treatment
                
NDC: 46122-044 | Form: CREAM
Manufacturer: Amerisource Bergen
Category: otc | Type: HUMAN OTC DRUG LABEL
Date: 20130630

ACTIVE INGREDIENTS: BENZOYL PEROXIDE 10 g/100 g
INACTIVE INGREDIENTS: MINERAL OIL; PETROLATUM; PROPYLENE GLYCOL; STEARYL ALCOHOL; POLYSORBATE 60; METHYLPARABEN; WATER

Drug Facts

Active ingredient Purpose

Benzoyl Peroxide 10%.................................................Acne Medication

Uses

- for the treatment and prevention of acne pimples

Warnings

- for external use only

Do not use if you have sensitive skin or are sensitive to benzoyl peroxide

When using this product

- avoid contact with the eyes, lips and mouth
- avoid contact with hair or dyed fabrics, including carpet and clothing which may be bleached by this product
- with other topical acne medications, at the same time or immediately following use of this product, increased dryness or irritation of the skin may occur. If this occurs, only one medication should be used unless directed by a doctor
- skin irritation may occur, characterized by redness, burning, itching, peeling or possibly swelling. More frequent use or concentration may aggravate skin irritation. Mild irritation may be reduced by using the product less frequently or in a lower concentration.

Stop use and ask a doctor if skin irritation becomes severe

Keep out of reach of children. In case of accidental ingestion, get medical help or contact a Poison Control Center immediately.

Directions

- cleanse the skin thoroughly before applying medication
- cover the entire affected area with a thin layer one to three times a day
- because excessive drying of the skin may occur, start with one application daily, then gradually increase to two to three times daily if needed or as direction by a doctor. If bothersome dryness or peeling occurs, reduce application to once a day or every other day.
- use to prevent new pimples from forming

Other information

- keep tightly closed
- keep away from heat

INACTIVE INGREDIENT

Inactive ingredients liquid paraffin, white petrolatum, cetanol, propylene glycol, stearyl alcohol, polyoxyehylencetylether, sorbitanmonostearate, polysorbate 60, methylparaben, butyl paraben, purified water

DOSAGE AND ADMINISTRATION

Distributed by

Amerisource Bergen

1300 Morris Drive

Chesterbrook, PA 19087

Made in Korea